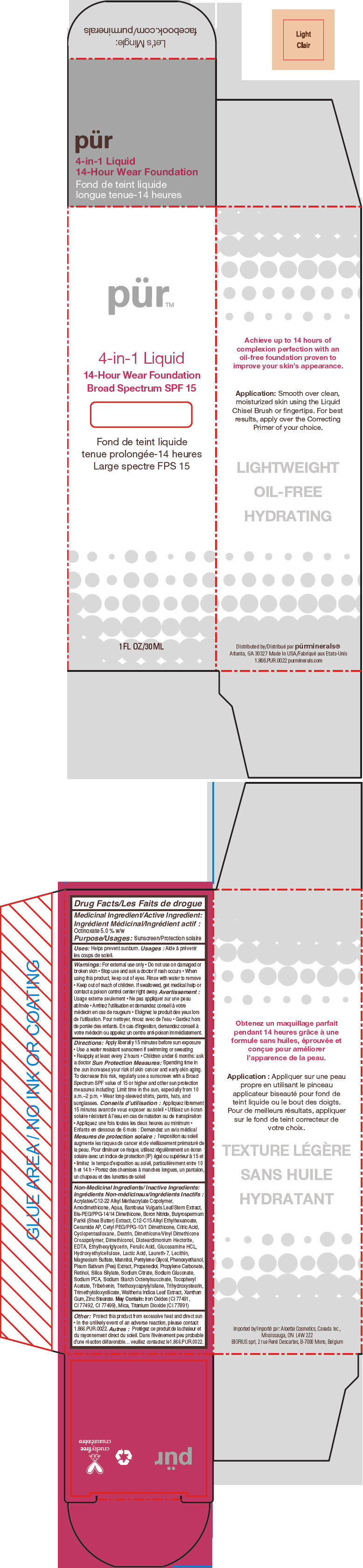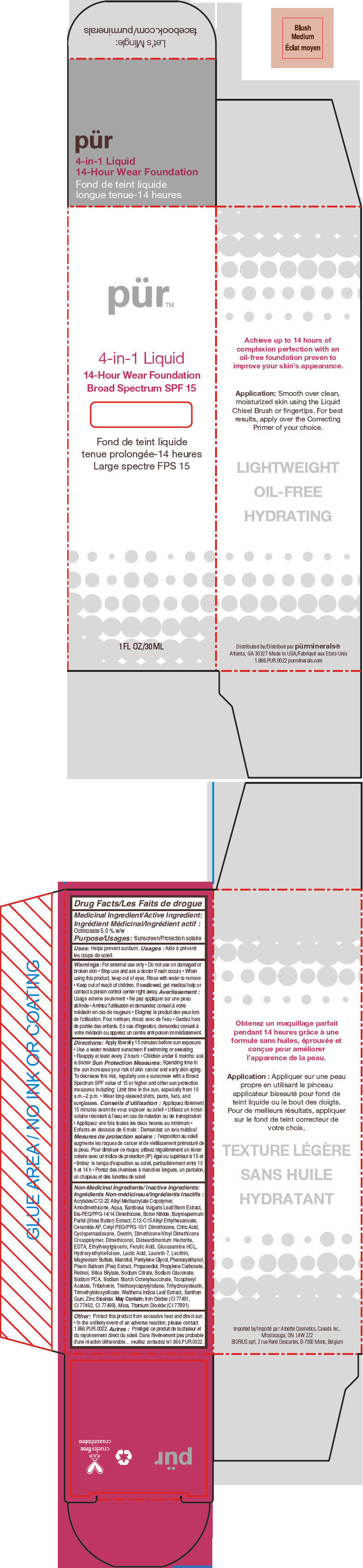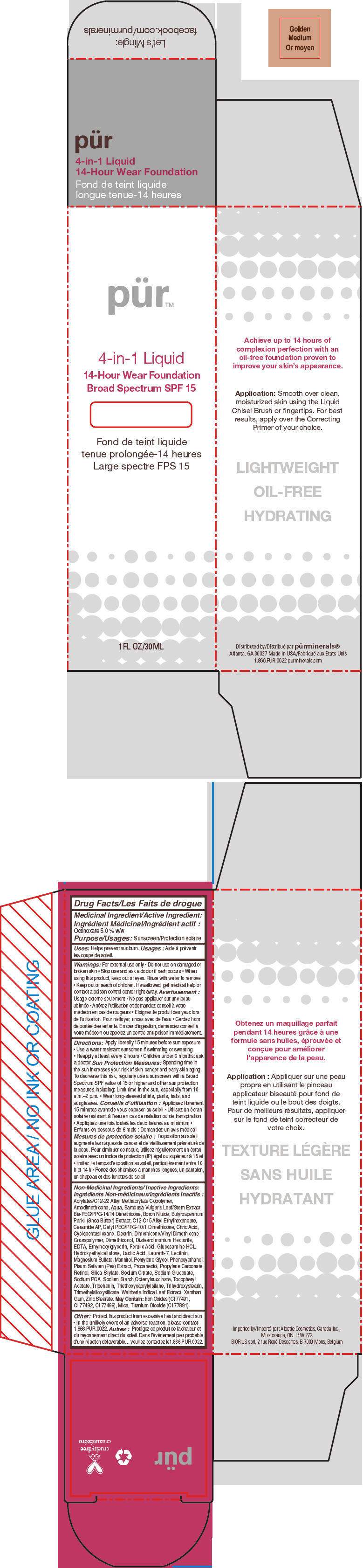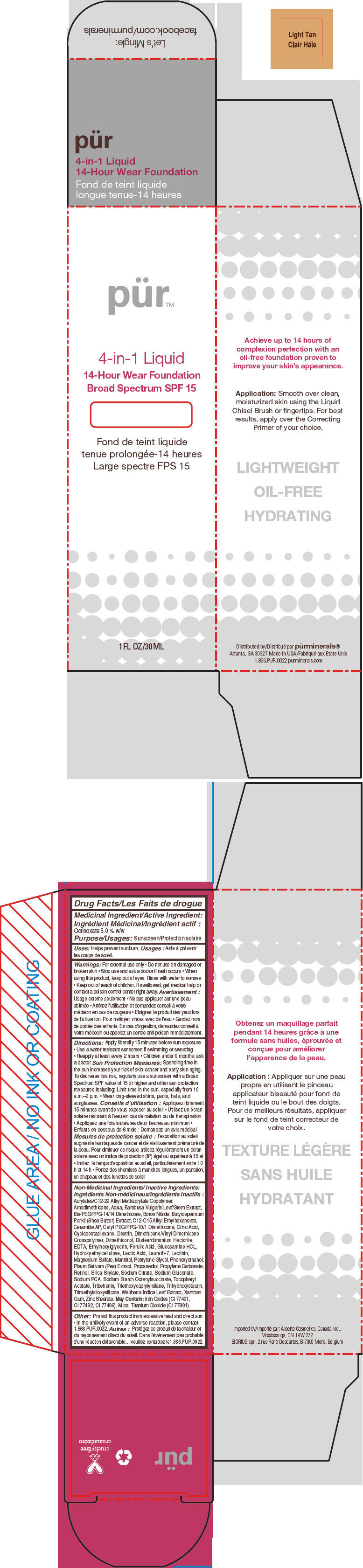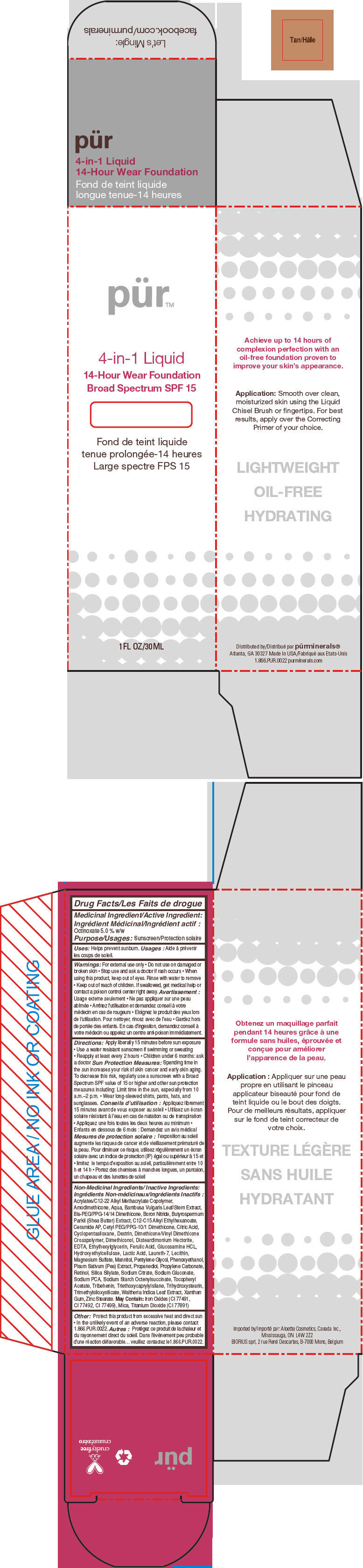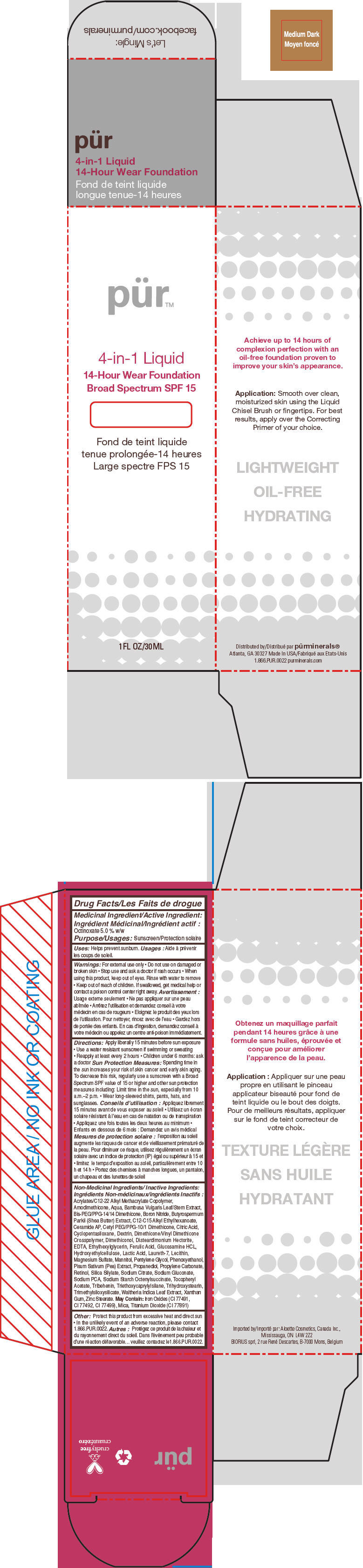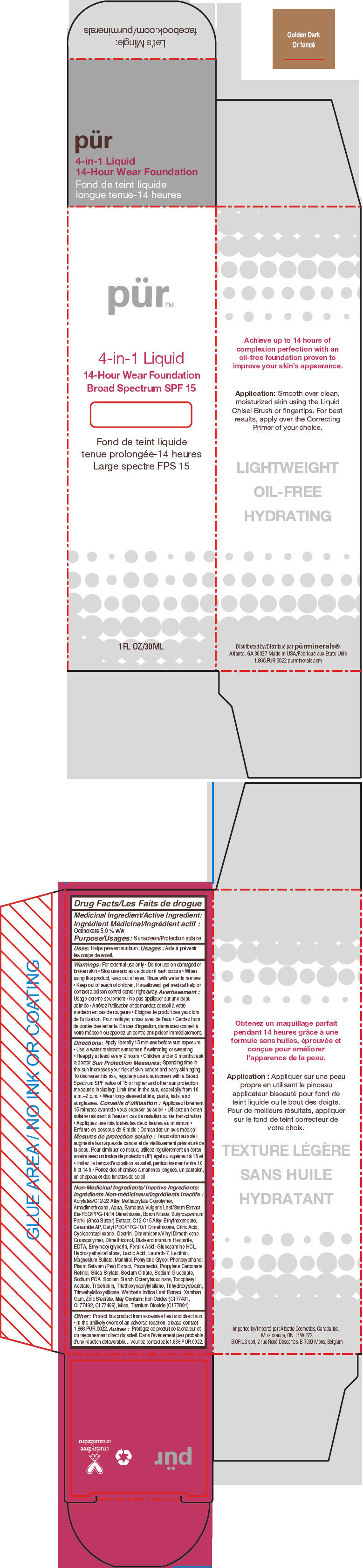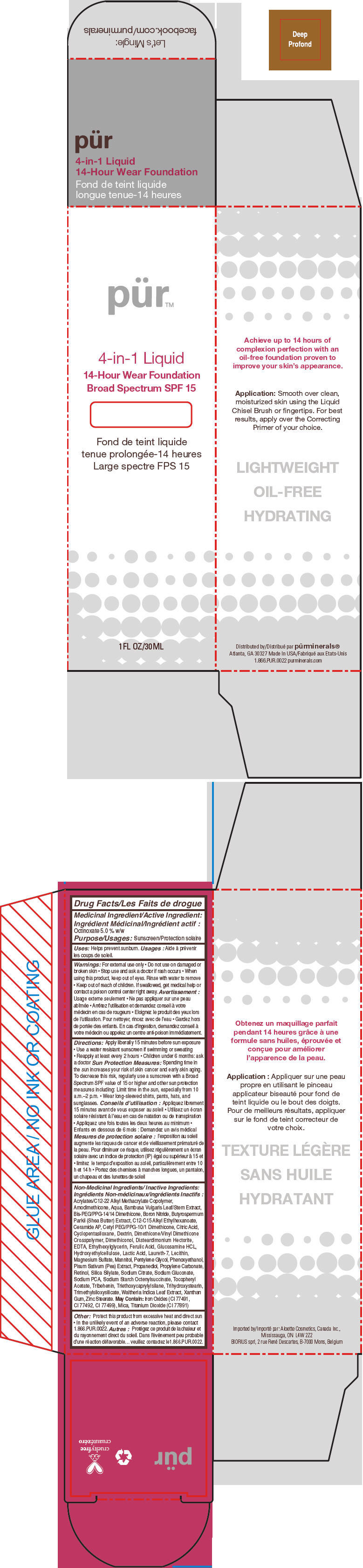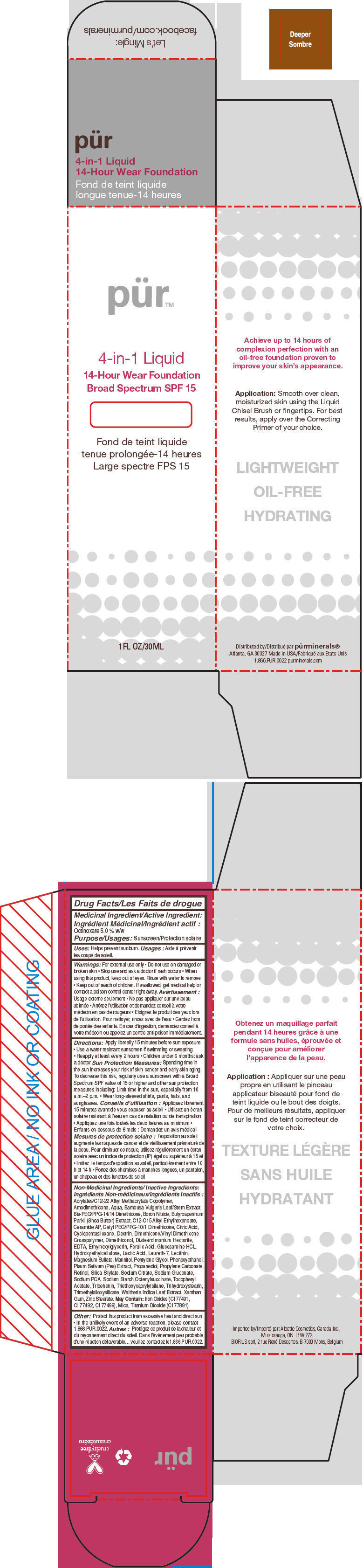 DRUG LABEL: Purminerals 4-in-1 14-Hour Wear Foundation Broad Spectrum SPF 15 (LIGHT)
NDC: 67345-0005 | Form: LIQUID
Manufacturer: Purminerals
Category: otc | Type: HUMAN OTC DRUG LABEL
Date: 20230125

ACTIVE INGREDIENTS: Octinoxate 50 mg/1 mL
INACTIVE INGREDIENTS: WATER; CYCLOMETHICONE 5; PROPANEDIOL; SODIUM PYRROLIDONE CARBOXYLATE; BORON NITRIDE; MAGNESIUM SULFATE, UNSPECIFIED FORM; ZINC STEARATE; PHENOXYETHANOL; MANNITOL; LAURETH-7; TRIBEHENIN; SHEANUT OIL; DISTEARDIMONIUM HECTORITE; GLUCOSAMINE HYDROCHLORIDE; TRIHYDROXYSTEARIN; TRIETHOXYCAPRYLYLSILANE; PEA; XANTHAN GUM; BAMBUSA VULGARIS TOP; .ALPHA.-TOCOPHEROL ACETATE; ETHYLHEXYLGLYCERIN; PROPYLENE CARBONATE; SODIUM GLUCONATE; PENTYLENE GLYCOL; LACTIC ACID, UNSPECIFIED FORM; CITRIC ACID MONOHYDRATE; SODIUM CITRATE, UNSPECIFIED FORM; ICODEXTRIN; RETINOL; WALTHERIA INDICA LEAF; FERULIC ACID; EDETIC ACID; CERAMIDE AP; MICA; TITANIUM DIOXIDE; FERRIC OXIDE RED

Pürminerals 4-in-1 Liquid 14-Hour Wear Foundation Broad Spectrum SPF 15

Drug Facts

Medicinal Ingredient/Active Ingredient

Octinoxate 5.0 % w/w

Purpose

Sunscreen

Uses

Helps prevent sunburn.

Warnings

For external use only

- Do not use on damaged or broken skin

- Stop use and ask a doctor if rash occurs

- When using this product, keep out of eyes. Rinse with water to remove

- Keep out of reach of children. If swallowed, get medical help or contact a poison control center right away

Directions

Apply liberally 15 minutes before sun exposure

- Use a water resistant sunscreen if swimming or sweating
- Reapply at least every 2 hours
- Children under 6 months: ask a doctor

Sun Protection Measures

Spending time in the sun increases your risk of skin cancer and early skin aging. To decrease this risk, regularly use a sunscreen with a Broad Spectrum SPF value of 15 or higher and other sun protection measures including: Limit time in the sun, especially from 10 a.m.–2 p.m.

- Wear long-sleeved shirts, pants, hats, and sunglasses.

Non-Medicinal Ingredients/ Inactive Ingredients

Acrylates/C12-22 Alkyl Methacrylate Copolymer, Amodimethicone, Aqua, Bambusa Vulgaris Leaf/Stem Extract, Bis-PEG/PPG-14/14 Dimethicone, Boron Nitride, Butyrospermum Parkii (Shea Butter) Extract, C12-C15 Alkyl Ethylhexanoate, Ceramide AP, Cetyl PEG/PPG-10/1 Dimethicone, Citric Acid, Cyclopentasiloxane, Dextrin, Dimethicone/Vinyl Dimethicone Crosspolymer, Dimethiconol, Disteardimonium Hectorite, EDTA, Ethylhexylglycerin, Ferulic Acid, Glucosamine HCL, Hydroxyethylcellulose, Lactic Acid, Laureth-7, Lecithin, Magnesium Sulfate, Mannitol, Pentylene Glycol, Phenoxyethanol, Pisum Sativum (Pea) Extract, Propanediol, Propylene Carbonate, Retinol, Silica Silylate, Sodium Citrate, Sodium Gluconate, Sodium PCA, Sodium Starch Octenylsuccinate, Tocopheryl Acetate, Tribehenin, Triethoxycaprylylsilane, Trihydroxystearin, Trimethylsiloxysilicate, Waltheria Indica Leaf Extract, Xanthan Gum, Zinc Stearate. May Contain: Iron Oxides (CI 77491, CI 77492, CI 77499), Mica, Titanium Dioxide (CI 77891)

Other

Protect this product from excessive heat and direct sun

- In the unlikely event of an adverse reaction, please contact 1.866.PUR.0022.

Distributed by pürminerals®
Atlanta, GA 30327

PRINCIPAL DISPLAY PANEL - 30 mL Bottle Carton - Light

pür™

4-in-1 Liquid

14-Hour Wear Foundation
Broad Spectrum SPF 15

1FL OZ/30ML

PRINCIPAL DISPLAY PANEL - 30 mL Bottle Carton - Blush Medium

pür™

4-in-1 Liquid

14-Hour Wear Foundation
Broad Spectrum SPF 15

1FL OZ/30ML

PRINCIPAL DISPLAY PANEL - 30 mL Bottle Carton - Golden Medium

pür™

4-in-1 Liquid

14-Hour Wear Foundation
Broad Spectrum SPF 15

1FL OZ/30ML

PRINCIPAL DISPLAY PANEL - 30 mL Bottle Carton - Light Tan

pür™

4-in-1 Liquid

14-Hour Wear Foundation
Broad Spectrum SPF 15

1FL OZ/30ML

PRINCIPAL DISPLAY PANEL - 30 mL Bottle Carton - Tan

pür™

4-in-1 Liquid

14-Hour Wear Foundation
Broad Spectrum SPF 15

1FL OZ/30ML

PRINCIPAL DISPLAY PANEL - 30 mL Bottle Carton - Medium Dark

pür™

4-in-1 Liquid

14-Hour Wear Foundation
Broad Spectrum SPF 15

1FL OZ/30ML

PRINCIPAL DISPLAY PANEL - 30 mL Bottle Carton - Golden Dark

pür™

4-in-1 Liquid

14-Hour Wear Foundation
Broad Spectrum SPF 15

1FL OZ/30ML

PRINCIPAL DISPLAY PANEL - 30 mL Bottle Carton - Deep

pür™

4-in-1 Liquid

14-Hour Wear Foundation
Broad Spectrum SPF 15

1FL OZ/30ML

PRINCIPAL DISPLAY PANEL - 30 mL Bottle Carton - Deeper

pür™

4-in-1 Liquid

14-Hour Wear Foundation
Broad Spectrum SPF 15

1FL OZ/30ML